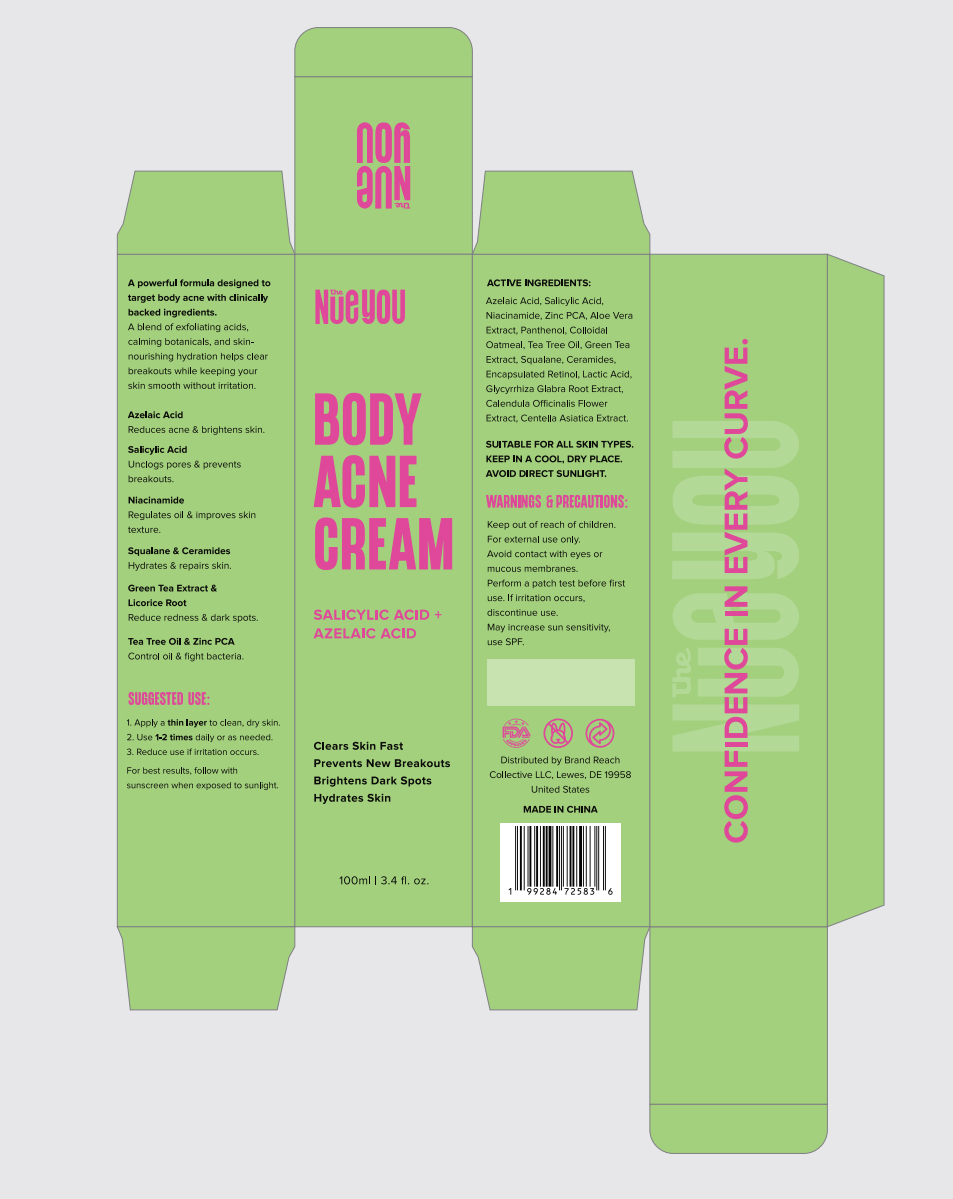 DRUG LABEL: The NueyOu
NDC: 85525-003 | Form: CREAM
Manufacturer: Brand Reach Collective LLC
Category: otc | Type: HUMAN OTC DRUG LABEL
Date: 20250416

ACTIVE INGREDIENTS: SALICYLIC ACID 20 mg/1 mL
INACTIVE INGREDIENTS: PANTHENOL; ZINC PCA; LACTIC ACID; SQUALANE; NIACINAMIDE; AZELAIC ACID

active

Salicylic Acid

inactive

SALICYLIC

ACIDZINC

PCALACTIC

ACIDSQUALANE
NIACINAMIDEAZELAIC ACID
PANTHENOL

PURPOSE

Clears Skin FastPrevents New BreakoutsBrightens Dark SpotsHydrates Skin

WARNINGS and PRECAUTIONS:

Keep out of reach of children.For external use only.Avoid contact with eyes ormucous membranes.Perform a patch test before firstuse. lf irritation occurs,discontinue use.May increase sun sensitivityuse SPF.

PREGAUTIONS:

Avoid contact with eyes ormucous membranes.

SUGGESTED USE:

Reduce use if irritation occurs.

WARNINGS G PREGAUTIONS:

Keep out of reach of children.

SUGGESTED USE:

Apply a thin layer to clean, dry skin

Indications & Usage Section

For the treatment of acne on the body. Helps clear up acne blemishes and prevent new ones from forming.

WARNINGS G PREGAUTIONS

Perform a patch test before firstuse. lf irritation occurs,discontinue use.

PACKAGE LABEL

A powerful formula designed totarget body acne with clinicallybacked ingredients.
A blend of exfoliating acids,
calming botanicals, and skin.
nourishing hydration helps clear
breakouts while keeping your
skin smooth without irritation.
Azelaic Acid
Reduces acne & brightens skin.
Salicylic Acid
Unclogs pores & prevents
breakouts.
Niacinamide
Regulates oil & improves skin
texture.
Squalane & Ceramides
Hydrates & repairs skin.
Green Tea Extract &
Licorice Root
Reduce redness & dark spots.
Tea Tree Oil & Zinc PCA
NUeyOU
BODY
ACNE
CREAM
SALICYLIC ACID +AZELAIC ACID
ACTIVE INGREDIENTS:
Azelaic Acid, Salicylic Acid,Niacinamide, Zinc PCA, Aloe VeraExtract,Panthenol,ColloidalOatmeal. Tea Tree Oil, Green TeaExtract,Squalane,Ceramides.
Encapsulated Retinol, Lactic AcidGlycyrrhiza Glabra Root Extract,Calendula Officinalis Flower
Extract, Centella Asiatica Extract.
SUITABLE FOR ALL SKIN TYPES
KEEP IN A COOL, DRY PLACE.
AVOID DIRECT SUNLIGHT.
WARNINGS G PRECAUTIONS:
Keep out of reach of children.
For external use only.
Avoid contact with eyes or
mucous membranes.
Perform a patch test before firstuse.lf irritation occurs.discontinue use.
May increase sun sensitivity.
use SPF.
Control oil & fight bacteria.
SUGGESTED USE:
1. Apply a thin layer to clean, dry skin.
2.Use 1-2 times daily or as needed.
3.Reduce use if irritation occurs.
For best results, follow with
sunscreen when exposed to sunlight
Clears Skin Fast
Prevents New BreakoutsBrightens Dark Spots
Hydrates Skin
Distributed by Brand Reach
Collective LLC, Lewes, DE 19958
United States
MADE IN CHINA